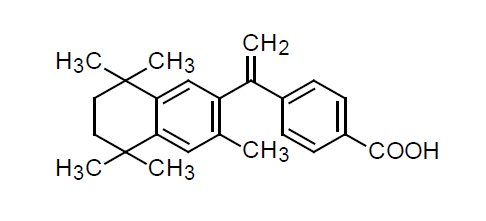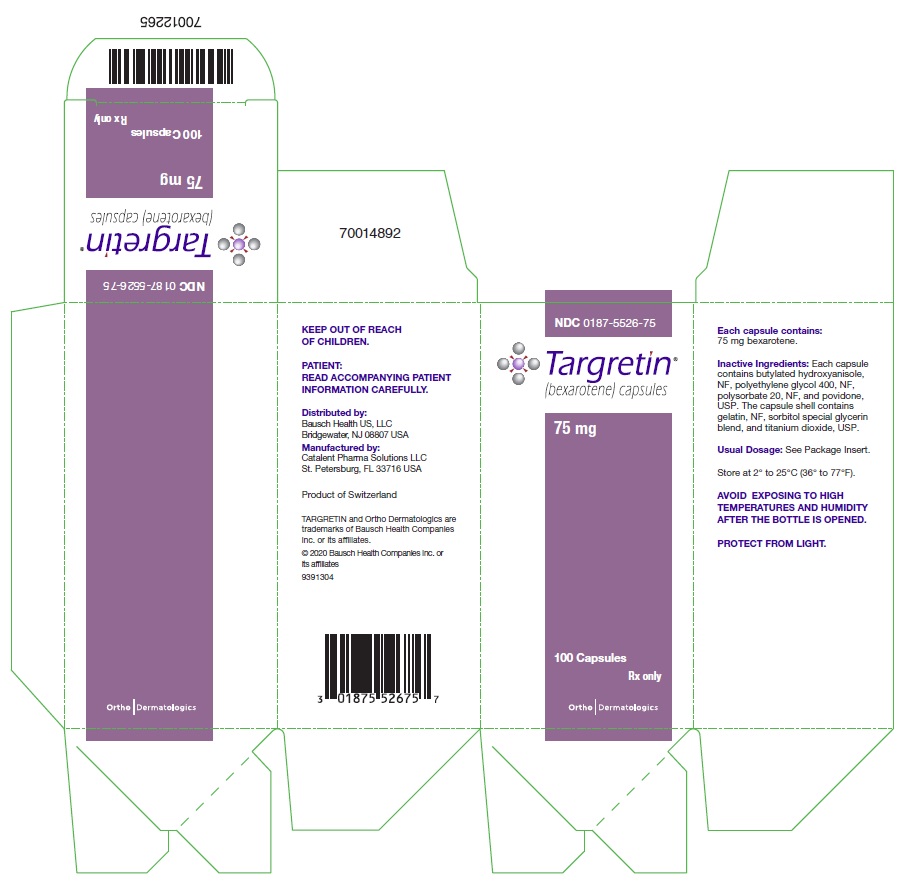 DRUG LABEL: Targretin
NDC: 0187-5526 | Form: CAPSULE, LIQUID FILLED
Manufacturer: Bausch Health US, LLC
Category: prescription | Type: HUMAN PRESCRIPTION DRUG LABEL
Date: 20200430

ACTIVE INGREDIENTS: BEXAROTENE 75 mg/1 1
INACTIVE INGREDIENTS: POLYETHYLENE GLYCOL 400; POLYSORBATE 20; BUTYLATED HYDROXYANISOLE; GLYCERIN; SORBITOL; 1,4-SORBITAN; MANNITOL; WATER; TITANIUM DIOXIDE; GELATIN, UNSPECIFIED; CROSPOVIDONE

HIGHLIGHTS OF PRESCRIBING INFORMATION

These highlights do not include all the information needed to use TARGRETIN safely and effectively. See full prescribing information for TARGRETIN.
TARGRETIN® (bexarotene) capsules, for oral use
Initial U.S. Approval: 1999

WARNING: BIRTH DEFECTS

See full prescribing information for complete boxed warning.

TARGRETIN is a member of the retinoid class of drugs that is associated with birth defects in humans. Bexarotene also caused birth defects when administered orally to pregnant rats. TARGRETIN must not be administered to a pregnant woman. (8.1)

1 INDICATIONS AND USAGE

TARGRETIN (bexarotene) is a retinoid indicated for the treatment of cutaneous manifestations of cutaneous T-cell lymphoma in patients who are refractory to at least one prior systemic therapy. (1)

2 DOSAGE AND ADMINISTRATION

- Recommended initial dose is 300 mg/m^2/day. (2)
- Take TARGRETIN as a single oral daily dose with a meal. (2)
- Dose Adjustment: May be adjusted to 200 mg/m^2/day then to 100 mg/m^2/day. (2)

3 DOSAGE FORMS AND STRENGTHS

Capsules: 75 mg (3)

4 CONTRAINDICATIONS

- Pregnancy (Boxed Warning, 4.1)
- Known hypersensitivity to bexarotene (4.2)

5 WARNINGS AND PRECAUTIONS

- Hyperlipidemia: TARGRETIN causes elevations in blood lipids. Obtain baseline values, monitor, and manage elevations during therapy by dose reduction, interruption, discontinuation and/or lipid lowering therapy. (5.1, 5.11)
- Pancreatitis: Interrupt TARGRETIN and evaluate if suspected. (5.2)
- Hepatotoxicity, Cholestasis, and Hepatic Failure: Interrupt or discontinue TARGRETIN and evaluate if liver chemistry tests exceed three times the upper limit of normal values. (5.3)
- Hypothyroidism: TARGRETIN therapy can cause hypothyroidism. Monitor and replace thyroid hormone if needed. (5.5)
- Neutropenia: Monitor for neutropenia. Reduce TARGRETIN dose or interrupt as indicated. (5.6)
- Photosensitivity: Minimize exposure to sunlight and artificial ultraviolet light during treatment. (5.10)

6 ADVERSE REACTIONS

The most common adverse reactions (greater than 10%) include: hyperlipidemia, hypercholesteremia, headache, hypothyroidism, asthenia, leukopenia, rash, nausea, infection, peripheral edema, abdominal pain, and dry skin. (6.1)

To report SUSPECTED ADVERSE REACTIONS, contact Bausch Health US, LLC at 1-800-321-4576 or FDA at 1-800-FDA-1088 or www.fda.gov/medwatch.

FULL PRESCRIBING INFORMATION

WARNING: BIRTH DEFECTS

TARGRETIN is a member of the retinoid class of drugs that is associated with birth defects in humans. Bexarotene also caused birth defects when administered orally to pregnant rats. TARGRETIN must not be administered to a pregnant woman. (8.1)

1 INDICATIONS AND USAGE

TARGRETIN® (bexarotene) Capsules are indicated for the treatment of cutaneous manifestations of cutaneous T-cell lymphoma in patients who are refractory to at least one prior systemic therapy.

2 DOSAGE AND ADMINISTRATION

The recommended initial dose of TARGRETIN is 300 mg/m^2/day (see Table 1). TARGRETIN should be taken as a single oral daily dose with a meal. For precautions to prevent pregnancy and birth defects in women of child-bearing potential [see Use in Specific Populations (8.1)].

Table 1: TARGRETIN Initial Dose Calculation According to Body Surface Area
Initial Dose Level (300 mg/m^2/day) |  | Number of 75 mg TARGRETIN Capsules
Body Surface Area; (m^2) | Total Daily Dose; (mg/day) | Number of 75 mg TARGRETIN Capsules
0.88 – 1.12 | 300 | 4
1.13 – 1.37 | 375 | 5
1.38 – 1.62 | 450 | 6
1.63 – 1.87 | 525 | 7
1.88 – 2.12 | 600 | 8
2.13 – 2.37 | 675 | 9
2.38 – 2.62 | 750 | 10

Dose Modification Guidelines: The 300 mg/m^2/day dose level of TARGRETIN may be adjusted to 200 mg/m^2/day then to 100 mg/m^2/day, or temporarily suspended, if necessitated by toxicity. When toxicity is controlled, doses may be carefully readjusted upward. If there is no tumor response after 8 weeks of treatment and if the initial dose of 300 mg/m^2/day is well tolerated, the dose may be escalated to 400 mg/m^2/day with careful monitoring.

Duration of Therapy: In clinical trials in CTCL, TARGRETIN was administered for up to 97 weeks.

TARGRETIN should be continued as long as the patient is deriving benefit.

3 DOSAGE FORMS AND STRENGTHS

Capsules: 75 mg, off-white, oblong soft gelatin capsules, imprinted with black ink “Targretin”.

4 CONTRAINDICATIONS

4.1 Pregnancy

TARGRETIN can cause fetal harm when administered to a pregnant female. TARGRETIN is a member of the retinoid class of drugs that is associated with birth defects in humans and is contraindicated in females who are pregnant. Bexarotene was also teratogenic and caused developmental mortality when administered orally to pregnant rats. If this drug is used during pregnancy or if the patient becomes pregnant while taking this drug, the patient should be advised of the potential risk to a fetus.

4.2 Hypersensitivity

TARGRETIN Capsules are contraindicated in patients with a known serious hypersensitivity to bexarotene or other components of the product.

5 WARNINGS AND PRECAUTIONS

5.1 Hyperlipidemia

TARGRETIN induces substantial elevations in lipids in most patients. About 70% of patients with CTCL who received an initial dose of >300 mg/m^2/day of TARGRETIN had fasting triglyceride levels greater than 2.5 times the upper limit of normal. About 55% had values over 800 mg/dL with a median of about 1200 mg/dL in those patients. Cholesterol elevations above 300 mg/dL occurred in approximately 60% and 75% of patients with CTCL who received an initial dose of 300 mg/m^2/day or greater than 300 mg/m^2/day, respectively. Decreases in high density lipoprotein (HDL) cholesterol to less than 25 mg/dL were seen in about 55% and 90% of patients receiving an initial dose of 300 mg/m^2/day or greater than 300 mg/m^2/day, respectively, of TARGRETIN. Monitor lipid changes and treat abnormalities during therapy. The effects on triglycerides, HDL cholesterol, and total cholesterol were reversible with cessation of therapy, and could generally be mitigated by dose reduction and/or concomitant antilipemic therapy.

Perform fasting blood lipid determinations before TARGRETIN therapy is initiated and weekly until the lipid response to TARGRETIN is established, which usually occurs within 2 to 4 weeks, and monitor at 8-week intervals thereafter. Fasting triglycerides should be normal or normalized with appropriate intervention prior to initiating TARGRETIN therapy. Maintain triglyceride levels below 400 mg/dL to reduce the risk of clinical sequelae [see Warnings and Precautions (5.2)]. If fasting triglycerides are elevated or become elevated during treatment, institute antilipemic therapy, and if necessary, reduce or interrupt the dose of TARGRETIN. In the 300 mg/m^2/day initial dose group, 60% of patients were given lipid lowering drugs. Atorvastatin was used in 48% (73/152) of patients with CTCL. Because of a potential drug-drug interaction, avoid gemfibrozil use with TARGRETIN [see Drug Interactions (7)].

5.2 Pancreatitis

Acute pancreatitis, including a fatal case, has been reported in four patients with CTCL and in six patients with non-CTCL cancers treated with TARGRETIN; the cases were associated with marked elevations of fasting serum triglycerides, the lowest being 770 mg/dL in one patient. One patient with advanced non-CTCL cancer died of pancreatitis. Interrupt TARGRETIN and evaluate if pancreatitis is suspected. Patients with CTCL who have risk factors for pancreatitis (e.g., prior pancreatitis, uncontrolled hyperlipidemia, excessive alcohol consumption, uncontrolled diabetes mellitus, biliary tract disease, and medications known to increase triglyceride levels or to be associated with pancreatic toxicity) may be at greater risk for pancreatitis associated with TARGRETIN [see Warnings and Precautions (5.1)].

5.3 Hepatotoxicity, Cholestasis, and Hepatic Failure

TARGRETIN caused elevations in liver chemistry tests (LFTs) in 5% (AST), 2% (ALT), and 0% (bilirubin) in patients with CTCL receiving an initial dose of 300 mg/m^2/day. In contrast, with an initial dose greater than 300 mg/m^2/day of TARGRETIN, the incidence of LFT elevations was higher at 7% (SGOT/AST), 9% (SGPT/ALT), and 6% (bilirubin). Two patients developed cholestasis, including one patient who died of liver failure. In clinical trials, elevated LFTs resolved within 1 month in 80% of patients following a decrease in dose or discontinuation of therapy. Obtain baseline LFTs and monitor LFTs after 1, 2, and 4 weeks of treatment initiation, and if stable, at least every 8 weeks thereafter during treatment. Interrupt or discontinue TARGRETIN if test results exceed three times the upper limit of normal values for AST, ALT, or bilirubin.

5.4 Hypothyroidism

TARGRETIN induces hypothyroidism in about half of all patients treated by causing a reversible reduction in levels of thyroid hormone (total thyroxine [total T4]) and thyroid-stimulating hormone (TSH). The incidence of decreases in TSH and total T4 were about 60% and 45%, respectively, in patients with CTCL receiving an initial dose of 300 mg/m^2/day. Hypothyroidism was reported as an adverse event in 29% of patients. Consider treatment with thyroid hormone supplementation in patients with hypothyroidism. In the 300 mg/m^2/day initial dose group, 37% of patients were treated with thyroid hormone replacement. Obtain baseline thyroid function tests and patients monitor during treatment.

5.5 Neutropenia

Leukopenia in the range of 1000 to <3000 WBC x 10^6/L occurred in 18% of patients with CTCL receiving an initial dose of 300 mg/m^2/day of TARGRETIN. Patients receiving an initial dose greater than 300 mg/m^2/day of TARGRETIN had an incidence of leukopenia of 43%. No patient with CTCL treated with TARGRETIN developed leukopenia of less than 1000 WBC x 10^6/L. The usual time to onset of leukopenia was 4 to 8 weeks after initiating TARGRETIN. The leukopenia observed in most patients was predominantly neutropenia. In the 300 mg/m^2/day initial dose group, the incidence of NCI Grade 3 and Grade 4 neutropenia, respectively, was 12% and 4%. The leukopenia and neutropenia experienced during TARGRETIN therapy resolved after dose reduction or discontinuation of treatment, on average within 30 days in 93% of the patients with CTCL and 82% of patients with non-CTCL cancers. Leukopenia and neutropenia were rarely associated with severe sequelae or serious adverse events. Obtain complete blood counts (CBC) at baseline and periodically during treatment.

5.6 Cataracts

Posterior subcapsular cataracts occurred in preclinical toxicity studies in rats and dogs administered bexarotene daily for 6 months. New cataracts or worsening of previous cataracts occurred in 15 of 79 patients who were monitored with serial slit lamp examinations. Because of the high prevalence and rate of cataract formation in older patient populations, the relationship of TARGRETIN and cataracts cannot be determined in the absence of an appropriate control group. Patients treated with TARGRETIN who experience visual difficulties should have an appropriate ophthalmologic evaluation.

5.7 Vitamin A Supplementation Hazard

In clinical studies, patients were advised to limit vitamin A intake to ≤15,000 IU/day. Because of the relationship of bexarotene to vitamin A, patients should be advised to limit vitamin A supplements to avoid potential additive toxic effects.

5.8 Hypoglycemia Risk in Patients with Diabetes Mellitus

In patients using insulin, agents enhancing insulin secretion (e.g., sulfonylureas), or insulin sensitizers (e.g., thiazolidinedione class), based on the mechanism of action, TARGRETIN could enhance the action of these agents, resulting in hypoglycemia. Hypoglycemia has not been associated with the use of TARGRETIN as monotherapy.

5.9 Photosensitivity

Retinoids as a class have been associated with photosensitivity. In vitro assays indicate that bexarotene is a potential photosensitizing agent. Phototoxicity manifested as sunburn and skin sensitivity to sunlight occurred in patients who were exposed to direct sunlight while receiving TARGRETIN. Advise patients to minimize exposure to sunlight and artificial ultraviolet light while receiving TARGRETIN.

5.10 Laboratory Tests

Before initiating TARGRETIN therapy, obtain a CBC, fasting lipid profile, liver function tests, and a thyroid profile. Fasting triglycerides should be normal or normalized with appropriate intervention prior to therapy. Monitor lab tests during TARGRETIN therapy as described above.

Hyperlipidemia usually occurs within the initial 2 to 4 weeks. Therefore, weekly lipid determinations are recommended during this interval. Subsequently, in patients not hyperlipidemic, determinations can be performed less frequently [see Warnings and Precautions (5.1)].

A white blood cell count with differential should be obtained at baseline and periodically during treatment. Baseline liver function tests should be obtained and should be carefully monitored after 1, 2, and 4 weeks of treatment initiation, and if stable, periodically thereafter during treatment. Baseline thyroid function tests should be obtained and then monitored during treatment as indicated [see Warnings and Precautions (5.3, 5.4, 5.5, 5.6)].

5.11 Drug/Laboratory Test Interactions

CA125 assay values in patients with ovarian cancer may be increased by TARGRETIN therapy.

6 ADVERSE REACTIONS

The following serious adverse reactions are discussed in greater detail in other sections of the prescribing information:

- Hyperlipidemia [see Warnings and Precautions (5.1)]
- Pancreatitis [see Warnings and Precautions (5.2)]
- Hepatotoxicity, Cholestasis, and Hepatic Failure [see Warnings and Precautions (5.3)]
- Hypothyroidism [see Warnings and Precautions (5.4)]
- Neutropenia [see Warnings and Precautions (5.5)]
- Cataracts [see Warnings and Precautions (5.6)]
- Vitamin A Supplementation Hazard [see Warnings and Precautions (5.7)]
- Hypoglycemia Risk in Patients with Diabetes Mellitus [see Warnings and Precautions (5.8)]
- Photosensitivity [see Warnings and Precautions (5.9)]
- Laboratory Tests [see Warnings and Precautions (5.10)]
- Drug/Laboratory Test Interactions [see Warnings and Precautions (5.11)]

6.1 Clinical Trials Experience

Because clinical trials are conducted under widely varying conditions, adverse reaction rates observed in the clinical trials of a drug cannot be directly compared to rates in the clinical trials of another drug and may not reflect the rates observed in practice.

The safety of TARGRETIN has been evaluated in two clinical trials of 152 patients with CTCL who received TARGRETIN for up to 97 weeks and in 352 patients in other trials. The mean duration of therapy for the 152 patients with CTCL was 166 days. The most common adverse events reported with an incidence of at least 10% in patients with CTCL treated at an initial dose of 300 mg/m^2/day of TARGRETIN are shown in Table 2. The events at least possibly related to treatment are lipid abnormalities (elevated triglycerides, elevated total and LDL cholesterol and decreased HDL cholesterol), hypothyroidism, headache, asthenia, rash, leukopenia, anemia, nausea, infection, peripheral edema, abdominal pain, and dry skin. Most adverse events occurred at a greater incidence in patients treated at starting doses of greater than 300 mg/m^2/day (see Table 2).

Adverse reactions leading to TARGRETIN dose reduction or discontinuation in at least two patients were hyperlipemia, neutropenia/leukopenia, diarrhea, fatigue/lethargy, hypothyroidism, headache, liver function test abnormalities, rash, pancreatitis, nausea, anemia, allergic reaction, muscle spasm, pneumonia, and confusion.

The NCI Grade 3 and NCI Grade 4 adverse reactions reported in two or more patients with CTCL treated at an initial dose of 300 mg/m^2/day of TARGRETIN (see Table 3) were hypertriglyceridemia, pruritus, headache, peripheral edema, leukopenia, rash, and hypercholesteremia. Most of these moderately severe or severe adverse events occurred at a higher rate in patients treated at starting doses of greater than 300 mg/m^2/day than in patients treated at a starting dose of 300 mg/m^2/day.

In patients with CTCL receiving an initial dose of 300 mg/m^2/day, the incidence of NCI Grade 3 or 4 elevations in triglycerides and total cholesterol was 28% and 25%, respectively (Table 4). In contrast, in patients with CTCL receiving greater than 300 mg/m^2/day, the incidence of NCI Grade 3 or 4 elevated triglycerides and total cholesterol was 45% and 45%, respectively. Other Grade 3 and 4 laboratory abnormalities are shown in Table 3.

In addition to the 152 patients enrolled in the two CTCL trials, 352 patients received TARGRETIN as monotherapy for various advanced malignancies at doses from 5 mg/m^2/day to 1000 mg/m^2/day. The common adverse reactions (incidence greater than 10%) were similar to those seen in patients with CTCL.

In the 504 patients (CTCL and non-CTCL) who received TARGRETIN as monotherapy, drug-related serious adverse reactions that were fatal, in one patient each, were acute pancreatitis, subdural hematoma, and liver failure.

In the patients with CTCL receiving an initial dose of 300 mg/m^2/day of TARGRETIN, adverse reactions reported at an incidence of less than 10% and not included in Tables 2 through 4 or discussed in other parts of labeling and possibly related to treatment were as follows:

Body as a Whole: chills, cellulitis, chest pain, breast pain, sepsis, and monilia infection.

Cardiovascular: hemorrhage, hypertension, angina pectoris, right heart failure, syncope, and tachycardia.

Digestive: constipation, dry mouth, flatulence, colitis, dyspepsia, cheilitis, gastroenteritis, gingivitis, liver failure, and melena.

Hemic and Lymphatic: eosinophilia, thrombocythemia, coagulation time increased, lymphocytosis, and thrombocytopenia.

Metabolic and Nutritional: LDH increased, creatinine increased, hypoproteinemia, hyperglycemia, weight decreased, weight increased, and amylase increased.

Musculoskeletal: arthralgia, myalgia, bone pain, myasthenia, and arthrosis.

Nervous: depression, agitation, ataxia, cerebrovascular accident, confusion, dizziness, hyperesthesia, hypesthesia, and neuropathy.

Respiratory: pharyngitis, rhinitis, dyspnea, pleural effusion, bronchitis, cough increased, lung edema, hemoptysis, and hypoxia.

Skin and Appendages: skin ulcer, acne, alopecia, skin nodule, macular papular rash, pustular rash, serous drainage, and vesicular bullous rash.

Special Senses: dry eyes, conjunctivitis, ear pain, blepharitis, corneal lesion, keratitis, otitis externa, and visual field defect.

Urogenital: albuminuria, hematuria, urinary incontinence, urinary tract infection, urinary urgency, dysuria, and kidney function abnormal.

Table 2: Adverse Events with Incidence ≥10% in CTCL Trials
 | Initial Assigned Dose Group; (mg/m^2/day)
 | 300 | >300
Body System | N=84 | N=53
Adverse Event (AE) [Preferred English term coded according to Ligand-modified COSTART 5 Dictionary.] , [Patients are counted at most once in each AE category.] | N (%) | N (%)
METABOLIC AND NUTRITIONAL DISORDERS
Hyperlipemia | 66 (79) | 42 (79)
Hypercholesteremia | 27 (32) | 33 (62)
Lactic dehydrogenase increased | 6 (7) | 7 (13)
BODY AS A WHOLE
Headache | 25 (30) | 22 (42)
Asthenia | 17 (20) | 24 (45)
Infection | 11 (13) | 12 (23)
Abdominal pain | 9 (11) | 2 (4)
Chills | 8 (10) | 7 (13)
Fever | 4 (5) | 9 (17)
Flu syndrome | 3 (4) | 7 (13)
Back pain | 2 (2) | 6 (11)
Infection bacterial | 1 (1) | 7 (13)
ENDOCRINE
Hypothyroidism | 24 (29) | 28 (53)
SKIN AND APPENDAGES
Rash | 14 (17) | 12 (23)
Dry skin | 9 (17) | 5 (9)
Exfoliative dermatitis | 8 (10) | 15 (28)
Alopecia | 3 (4) | 6 (11)
HEMIC AND LYMPHATIC SYSTEM
Leukopenia | 14 (17) | 25 (47)
Anemia | 5 (6) | 13 (25)
Hypochromic anemia | 3 (4) | 7 (13)
DIGESTIVE SYSTEM
Nausea | 13 (16) | 4 (8)
Diarrhea | 6 (7) | 22 (42)
Vomiting | 3 (4) | 7 (13)
Anorexia | 2 (2) | 12 (23)
CARDIOVASCULAR SYSTEM
Peripheral edema | 11 (13) | 6 (11)
NERVOUS SYSTEM
Insomnia | 4 (5) | 6 (11)

Table 3: Incidence of Moderately Severe and Severe Adverse Events

Reported in at Least Two Patients (CTCL Trials)

 | Initial Assigned Dose Group (mg/m^2/day)
 | 300 (N=84) |  | >300 (N=53)
 | Mod Sev | Severe | Mod Sev | Severe
Body System
Adverse Event (AE) [Preferred English term coded according to Ligand-modified COSTART 5 Dictionary.] , [Patients are counted at most once in each AE category. Patients are classified by the highest severity within each row.] | N (%) | N (%) | N (%) | N (%)
BODY AS A WHOLE
Asthenia | 1 (1) | 0 (0) | 11 (21) | 0 (0)
Headache | 3 (4) | 0 (0) | 5 (9) | 1 (2)
Infection bacterial | 1 (1) | 0 (0) | 0 (0) | 2 (4)
CARDIOVASCULAR SYSTEM
Peripheral edema | 2 (2) | 1 (1) | 0 (0) | 0 (0)
DIGESTIVE SYSTEM
Anorexia | 0 (0) | 0 (0) | 3 (6) | 0 (0)
Diarrhea | 1 (1) | 1 (1) | 2 (4) | 1 (2)
Pancreatitis | 1 (1) | 0 (0) | 3 (6) | 0 (0)
Vomiting | 0 (0) | 0 (0) | 2 (4) | 0 (0)
ENDOCRINE
Hypothyroidism | 1 (1) | 1 (1) | 2 (4) | 0 (0)
HEMIC AND LYMPHATIC SYSTEM
Leukopenia | 3 (4) | 0 (0) | 6 (11) | 1 (2)
METABOLIC AND NUTRITIONAL DISORDERS
Bilirubinemia | 0 (0) | 1 (1) | 2 (4) | 0 (0)
Hypercholesteremia | 2 (2) | 0 (0) | 5 (9) | 0 (0)
Hyperlipemia | 16 (19) | 6 (7) | 17 (32) | 5 (9)
SGOT/AST increased | 0 (0) | 0 (0) | 2 (4) | 0 (0)
SGPT/ALT increased | 0 (0) | 0 (0) | 2 (4) | 0 (0)
RESPIRATORY SYSTEM
Pneumonia | 0 (0) | 0 (0) | 2 (4) | 2 (4)
SKIN AND APPENDAGES
Exfoliative dermatitis | 0 (0) | 1 (1) | 3 (6) | 1 (2)
Rash | 1 (1) | 2 (2) | 1 (2) | 0 (0)

Table 4: Treatment-Emergent Abnormal Laboratory Values in CTCL Trials

 | Initial Assigned Dose (mg/m^2/day)
 | 300 |  | >300
 | N=83 [Number of patients with at least one analyte value post-baseline.] |  | N=53
Analyte | Grade 3 [Adapted from NCI Common Toxicity Criteria, Grade 3 and 4, Version 2.0. Patients are considered to have had a Grade 3 or 4 value if either of the following occurred: a) Value becomes Grade 3 or 4 during the study; b) Value is abnormal at baseline and worsens to Grade 3 or 4 on study, including all values beyond study drug discontinuation, as defined in data handling conventions.]; (%) | Grade 4; (%) | Grade 3; (%) | Grade 4; (%)
Triglycerides [The denominator used to calculate the incidence rates for fasting Total Cholesterol and Triglycerides were N=75 for the 300 mg/m^2/day initial dose group and N=44 for the >300 mg/m^2/day initial dose group.] | 21 | 7 | 32 | 14
Total cholesterol | 19 | 7 | 16 | 30
Alkaline phosphatase | 1 | 0 | 0 | 2
Hyperglycemia | 1 | 0 | 6 | 0
Hypocalcemia | 1 | 0 | 0 | 0
Hyponatremia | 1 | 0 | 9 | 0
SGPT/ALT | 1 | 0 | 2 | 2
Hyperkalemia | 0 | 0 | 2 | 0
Hypernatremia | 0 | 1 | 0 | 0
SGOT/AST | 0 | 0 | 2 | 2
Total bilirubin | 0 | 0 | 0 | 2
ANC decreased | 12 | 4 | 19 | 8
ALC decreased | 7 | 0 | 15 | 0
WBC decreased | 4 | 0 | 11 | 0
Hemoglobin decreased | 0 | 0 | 2 | 0

The safety profile from the one post-approval trial with 59 subjects was generally comparable to that of the pivotal trials with the exception of serious adverse events hypertriglyceridemia, neutropenia and bone marrow failure which were observed more frequently in the TARGRETIN 300 mg/m^2/day group than in the TARGRETIN 150 mg/m^2/day group.

Severe hypertriglyceridemia (≥800 mg/dL) was not seen in any subject in the lower dosage arm.

The most common AEs by preferred term in either the TARGRETIN 300 or 150 mg/m^2/day treatment group were as follows: hypertriglyceridemia (18 subjects [62.1%] and 17 subjects [56.7%], respectively); hypothyroidism (15 subjects [51.7%] and 13 subjects [43.3%], respectively); headache (9 subjects [31.0%] and 7 subjects [23.3%], respectively); hypercholesterolemia (8 subjects [27.6%] and 7 subjects [23.3%], respectively); neutropenia (7 subjects [24.1%] and 2 subjects [6.7%], respectively); and skin exfoliation (5 subjects [17.2%] and 5 subjects [16.7%], respectively).

Higher percentage of subjects in the TARGRETIN 300 mg/m^2/day group than in the TARGRETIN 150 mg/m^2/day group experienced SAEs (13 subjects [44.8%] vs 11 subjects [36.7%], respectively.

Of the SAEs of special interest, there were more events in the TARGRETIN 300 mg/m^2/day group than in TARGRETIN 150 mg/m^2/day group of bone marrow failure (3 [10.3%] vs 1 [3.3%, respectively]), neutropenia (3 [10.3%] vs 0 [0%], respectively), and hypertriglyceridemia (9 [31%] vs 2 [6.7%], respectively).

7 DRUG INTERACTIONS

Effect of Other Drugs on TARGRETIN

Gemfibrozil: Concomitant administration of TARGRETIN and gemfibrozil resulted in increases in plasma concentrations of bexarotene. Concomitant administration of gemfibrozil with TARGRETIN is not recommended.

Effect of TARGRETIN on Other Drugs

TARGRETIN may be an inducer for the CYP3A4 enzymes, and may reduce plasma concentrations of other substrates metabolized by CYP3A4. Drug products which may be affected include oral or other systemic hormonal contraceptives. Thus, if treatment with TARGRETIN is intended for a female with reproductive potential, it is strongly recommended that a non-hormonal contraception be considered. [see Use in Specific Populations (8.3), Clinical Pharmacology (12.3)].

Laboratory Test Interference

CA125 assay values in patients with ovarian cancer may be increased by TARGRETIN therapy.

8 USE IN SPECIFIC POPULATIONS

8.1 Pregnancy

Risk Summary

TARGRETIN, a retinoid, can cause fetal harm based on findings from animal studies when administered to a pregnant female and is contraindicated during pregnancy. Bexarotene was teratogenic and caused developmental mortality in rats following oral administration during organogenesis [see Data]. TARGRETIN must not be given to a pregnant female or a female who intends to become pregnant. If pregnancy does occur during treatment with TARGRETIN, immediately discontinue the drug and advise the pregnant female of the potential risk to a fetus.

The background risk of major birth defects and miscarriage for the indicated populations is unknown. However, the background risk in the U.S. general population of major birth defects is 2-4% and of miscarriage is 15-20% of clinically recognized pregnancies.

Data

Animal Data

Bexarotene caused malformations when administered orally to pregnant rats during days 7-17 of gestation. Developmental abnormalities included incomplete ossification at 4 mg/kg/day and cleft palate, depressed eye bulge/microphthalmia, and small ears at 16 mg/kg/day. The plasma AUC of bexarotene in rats at 4 mg/kg/day is approximately one third the AUC in humans at the recommended daily dose. At doses greater than 10 mg/kg/day, bexarotene caused developmental mortality. The no effect dose for fetal effects in rats was 1 mg/kg/day (producing an AUC approximately one sixth of the AUC at the recommended human daily dose).

8.2 Lactation

Risk Summary

There is no information regarding the presence of TARGRETIN in human milk, the effects on the breast fed infant, or the effects on milk production. Because many drugs are excreted in human milk and because of the potential for serious adverse reactions in nursing infants from TARGRETIN, discontinue breastfeeding during treatment with TARGRETIN.

8.3 Females and Males of Reproductive Potential

Pregnancy Testing

Obtain a negative serum pregnancy test (e.g., serum beta-human chorionic gonadotropin [beta-HCG]) with a sensitivity of at least 50 mIU/L within 1 week prior to TARGRETIN therapy. Obtain another pregnancy test at monthly intervals while the patient remains on TARGRETIN.

Contraception

Females

TARGRETIN can cause fetal harm when administered to a pregnant female [see Use in Specific Populations (8.1)]. Females of reproductive potential should be advised to avoid becoming pregnant when TARGRETIN is used. Effective contraception must be used for 1 month prior to the initiation of therapy, during therapy and for at least 1 month following discontinuation of therapy; it is recommended that two reliable forms of contraception be used simultaneously unless abstinence is the chosen method. Bexarotene can potentially induce metabolic enzymes and thereby theoretically reduce the plasma concentrations of oral or other systemic hormonal contraceptives [see Drug Interactions (7)]. Thus, if treatment with TARGRETIN is intended in a female with reproductive potential, it is strongly recommended that one of the two reliable forms of contraception should be non-hormonal. TARGRETIN therapy should be initiated on the second or third day of a normal menstrual period. No more than a 1-month supply of TARGRETIN should be given to the patient so that the results of pregnancy testing can be assessed and counseling regarding avoidance of pregnancy and birth defects can be reinforced.

Males

Male patients with sexual partners who are pregnant, possibly pregnant, or who could become pregnant must use condoms during sexual intercourse while taking TARGRETIN and for at least 1 month after the last dose of drug.

8.4 Pediatric Use

Safety and effectiveness of TARGRETIN in pediatric patients have not been established.

8.5 Geriatric Use

Of the total patients with CTCL in clinical trials of TARGRETIN, 64% were 60 years or older, while 33% were 70 years or older. No overall differences in safety were observed between patients 70 years or older and younger patients, but greater sensitivity of some older individuals to TARGRETIN cannot be ruled out. Responses to TARGRETIN were observed across all age group decades, without preference for any individual age group decade.

8.6 Hepatic Impairment

No specific studies have been conducted with TARGRETIN in subjects with hepatic impairment. Hepatic impairment is expected to lead to decreased clearance [see Clinical Pharmacology (12.3)]. If TARGRETIN is used in patients with hepatic impairment, monitor for signs of toxicity that may be due to increased exposure.

10 OVERDOSAGE

Doses up to 1000 mg/m^2/day of TARGRETIN have been administered in short-term trials in patients with advanced cancer without acute toxic effects. Single doses of 1500 mg/kg and 720 mg/kg were tolerated without significant toxicity in rats and dogs, respectively. These doses are approximately 30 and 50 times, respectively, the recommended human dose on a mg/m^2 basis.

11 DESCRIPTION

TARGRETIN® (bexarotene) Capsules contain bexarotene, a member of a subclass of retinoids that selectively activate retinoid X receptors (RXRs). These retinoid receptors have biologic activity distinct from that of retinoic acid receptors (RARs).

The chemical name of bexarotene is 4-[1-(5,6,7,8-tetrahydro-3,5,5,8,8-pentamethyl-2-naphthalenyl)ethenyl]benzoic acid, and the structural formula is as follows:

Bexarotene is an off-white to white powder with a molecular weight of 348.48 and a molecular formula of C24H28O2. It is insoluble in water and slightly soluble in vegetable oils and ethanol, USP.

Each TARGRETIN capsule contains 75 mg of bexarotene for oral administration. It also contains the following inactive ingredients: butylated hydroxyanisole, NF, polyethylene glycol 400, NF, polysorbate 20, NF, and povidone, USP. The capsule shell contains gelatin, NF, sorbitol special glycerin blend, and titanium dioxide, USP.

12 CLINICAL PHARMACOLOGY

12.1 Mechanism of Action

Bexarotene selectively binds and activates retinoid X receptor subtypes (RXRα, RXRß, RXRγ). RXRs can form heterodimers with various receptor partners such as retinoic acid receptors (RARs), vitamin D receptor, thyroid receptor, and peroxisome proliferator activator receptors (PPARs). Once activated, these receptors function as transcription factors that regulate the expression of genes that control cellular differentiation and proliferation. Bexarotene inhibits the growth in vitro of some tumor cell lines of hematopoietic and squamous cell origin. It also induces tumor regression in vivo in some animal models. The exact mechanism of action of bexarotene in the treatment of cutaneous T-cell lymphoma (CTCL) is unknown.

12.3 Pharmacokinetics

Terminal half-life of bexarotene is approximately 7 hours. Studies in patients with advanced malignancies show approximate single dose linearity within the therapeutic range.

Absorption

After oral administration of TARGRETIN, bexarotene is absorbed with a Tmax of about 2 hours. Plasma bexarotene AUC and Cmax values resulting from a 75 to 300 mg dose were 35% and 48% higher, respectively, after a fat-containing meal than after a glucose solution.

Distribution

Bexarotene is highly bound (>99%) to plasma proteins. The plasma proteins to which bexarotene binds have not been elucidated, and the ability of bexarotene to displace drugs bound to plasma proteins and the ability of drugs to displace bexarotene binding have not been studied.

Elimination

Metabolism

Four bexarotene metabolites have been identified in plasma: 6- and 7-hydroxy-bexarotene and 6- and 7-oxo-bexarotene. In vitro studies suggest that cytochrome P450 3A4 is the major cytochrome P450 responsible for formation of the oxidative metabolites and that the oxidative metabolites may be glucuronidated. The oxidative metabolites are active in in vitro assays of retinoid receptor activation, but the relative contribution of the parent and any metabolites to the efficacy and safety of TARGRETIN is unknown.

Excretion

The renal elimination of bexarotene and its metabolites was examined in patients with Type 2 diabetes mellitus. Urinary elimination of bexarotene and its known metabolites is a minor excretory pathway (<1% of administered dose).

Pharmacokinetics in Specific Populations

Age: Based on the population pharmacokinetic analysis of data for 232 patients aged ≥65 years and 343 patients aged <65 years, age has no statistically significant effect on bexarotene pharmacokinetics.

Body Weight and Gender: Based on the population pharmacokinetics analysis of data for 614 patients with a weight range of 26 to 145 kg, the bexarotene apparent clearance increases with increasing body weight. Gender has no statistically significant effect on bexarotene pharmacokinetics.

Race: Based on the population pharmacokinetic analysis of data for 540 Caucasian and 44 Black patients, bexarotene pharmacokinetics are similar in Blacks and Caucasians. There are insufficient data to evaluate potential differences in the pharmacokinetics of bexarotene for other races.

Renal Impairment: No formal studies have been conducted with TARGRETIN in patients with renal impairment. Urinary elimination of bexarotene and its known metabolites is a minor excretory pathway (<1% of administered dose), but because renal impairment can result in significant protein binding changes, pharmacokinetics may be altered in patients with renal impairment.

Hepatic Impairment: No specific studies have been conducted with TARGRETIN in patients with hepatic impairment. Because less than 1% of the dose is excreted in the urine unchanged and there is in vitro evidence of extensive hepatic contribution to bexarotene elimination, hepatic impairment would be expected to lead to greatly decreased clearance.

Drug Interactions

Effect of Other Drugs on TARGRETIN

CYP3A4 Inhibitors/Inducers: In a clinical study, concomitant administration of multiple doses of ketoconazole with TARGRETIN did not alter bexarotene plasma concentrations. This suggests that bexarotene elimination is not dependent on CYP3A4 metabolism.

Paclitaxel plus Carboplatin: The co-administration of paclitaxel (200 mg/m^2 IV dose over 3 hours) plus carboplatin (at a dose expected to achieve an AUC of 6 mg●min/mL) with TARGRETIN (400 mg/m^2 orally once daily) increased the exposure to bexarotene (AUC0-24 and Cmax) by 2-fold compared to TARGRETIN alone.

Atorvastatin: Bexarotene concentrations were not affected by concomitant atorvastatin administration.

Effect of TARGRETIN on Other Drugs

Bexarotene did not significantly inhibit the following enzymes in human liver microsomes: CYP1A2, CYP2A6, CYP2C9, CYP2C19, CYP2D6, CYP2E1 and CYP3A4. In vitro data suggested a potential for bexarotene to inhibit CYP2C8 and induce CYP3A4.

Atorvastatin: The exposure (AUC) to atorvastatin (a substrate for CYP3A4) decreased by half when atorvastatin was co-administered with TARGRETIN (400 mg/m^2 orally once daily).

Tamoxifen: Based on interim data, concomitant administration of TARGRETIN and tamoxifen resulted in approximately a 35% decrease in plasma concentrations of tamoxifen, possibly through induction of CYP3A4 by bexarotene.

Paclitaxel: The exposure (AUC) to paclitaxel (a substrate for CYP3A4 and CYP2C8) decreased by 19% when paclitaxel (200 mg/m^2 IV dose over 3 hours) was co-administered with TARGRETIN (400 mg/m^2 orally once daily).

Carboplatin: The co-administration of TARGRETIN (400 mg/m^2 orally once daily) had no effect on the exposure to free or total carboplatin.

13 NONCLINICAL TOXICOLOGY

13.1 Carcinogenesis, Mutagenesis, Impairment of Fertility

Long-term studies in animals to assess the carcinogenic potential of bexarotene have not been conducted. Bexarotene is not mutagenic to bacteria (Ames assay) or mammalian cells (mouse lymphoma assay). Bexarotene was not clastogenic in vivo (micronucleus test in mice).

No formal fertility studies were conducted with bexarotene. Bexarotene caused testicular degeneration when oral doses of 1.5 mg/kg/day were given to dogs for 91 days (producing an AUC of approximately one fifth the AUC at the recommended human daily dose).

14 CLINICAL STUDIES

TARGRETIN was evaluated in two clinical trials in 152 patients with advanced and early stage cutaneous T-cell lymphoma (CTCL) in two multicenter, open-label, historically controlled clinical trials conducted in the U.S., Canada, Europe, and Australia.

The advanced disease patients had disease refractory to at least one prior systemic therapy (median of two, range 1 to 6 prior systemic therapies) and had been treated with a median of five (range 1 to 11) prior systemic, irradiation, and/or topical therapies. Early disease patients were intolerant to, had disease that was refractory to, or had reached a response plateau of 6 months on, at least two prior therapies. The patients entered had been treated with a median of 3.5 (range 2 to 12) therapies (systemic, irradiation, and/or topical).

The two clinical trials enrolled a total of 152 patients, 102 of whom had disease refractory to at least one prior systemic therapy, 90 with advanced disease and 12 with early disease. This is the patient population for whom TARGRETIN is indicated.

Patients were initially treated with a starting dose of 650 mg/m^2/day with a subsequent reduction of starting dose to 500 mg/m^2/day. Neither of these starting doses was tolerated, and the starting dose was then reduced to 300 mg/m^2/day. If, however, a patient on 300 mg/m^2/day of TARGRETIN showed no response after 8 or more weeks of therapy, the dose could be increased to 400 mg/m^2/day.

Tumor response was assessed in both trials by observation of up to five baseline-defined index lesions using a Composite Assessment of Index Lesion Disease Severity (CA). This endpoint was based on a summation of the grades, for all index lesions, of erythema, scaling, plaque elevation, hypopigmentation or hyperpigmentation, and area of involvement. Also considered in response assessment was the presence or absence of cutaneous tumors and extracutaneous disease manifestations.

All tumor responses required confirmation over at least two assessments separated by at least 4 weeks. A partial response was defined as an improvement of at least 50% in the index lesions without worsening, or development of new cutaneous tumors or non-cutaneous manifestations. A complete clinical response required complete disappearance of all manifestations of disease, but did not require confirmation by biopsy.

At the initial dose of 300 mg/m^2/day, 1/62 (1.6%) of patients had a complete clinical tumor response and 19/62 (30%) of patients had a partial tumor response. The rate of relapse (25% increase in CA or worsening of other aspects of disease) in the 20 patients who had a tumor response was 6/20 (30%) over a median duration of observation of 21 weeks, and the median duration of tumor response had not been reached. Responses were seen as early as 4 weeks and new responses continued to be seen at later visits.

In one post-approval clinical trial with a total of 59 subjects (29 in 300 mg/m^2/day dose group and 30 in the 150 mg/m^2/day dose), the objective response rate was higher in the TARGRETIN 300 mg/m^2/day group than in the TARGRETIN 150 mg/m^2/day group with respect to the CA (34.5% vs 23.3%), Physicians Global Assessment (PGA) (37.9% vs 20.0%), and percent BSA involvement (34.5% vs 23.3%).

The median duration of response in the TARGRETIN 300 mg/m^2/day group based on the CA, PGA, and percent BSA involvement was 86.5 days, 72.0 days and 60.0 days, respectively. While in the TARGRETIN 150 mg/m^2/day group the median duration of response based on the CA, PGA, and percent BSA involvement was 55 days, 119.0 days and 118.0 days, respectively.

The median time to cutaneous tumor response (the time to cutaneous tumor response for a given subject is defined as the time interval from the first day of TARGRETIN treatment to the time of the first observation when the subject with subsequent confirmation of response meets criteria for CR, CCR or PR) in the TARGRETIN 300 mg/m^2/day group based on the CA, PGA, and percent BSA involvement was 85 days, 98 days and 117.5 days, respectively. While in the TARGRETIN 150 mg/m^2/day group the median time to cutaneous tumor response based on the CA, PGA, and percent BSA involvement was 87 days, 57 days and 57 days, respectively. In the TARGRETIN 300 mg/m^2/day group, the median time to cutaneous tumor progression based on the CA, PGA, and percent BSA involvement was 77.5, 115.5, and 88.0 days, respectively. In the TARGRETIN 150 mg/m^2/day group, the median time to cutaneous tumor progression was 203.0 days based on the CA and 86.0 days based on percent BSA involvement; no subject in this treatment group had cutaneous tumor progression based on the PGA.

16 HOW SUPPLIED/STORAGE AND HANDLING

TARGRETIN® (bexarotene) Capsules are supplied as 75 mg off-white, oblong soft gelatin capsules, imprinted with “Targretin”, in high density polyethylene bottles with child-resistant closures.

Bottles of 100 capsules: NDC 0187-5526-75

Store at 2° to 25°C (36° to 77°F). Avoid exposing to high temperatures and humidity after the bottle is opened. Protect from light.

17 PATIENT COUNSELING INFORMATION

Advise the patient to read the FDA-approved patient labeling (Patient Information).

Inform the patient or caregiver about the following:

Birth Defects

Advise patients that TARGRETIN is contraindicated in pregnancy [see Contraindications (4.1)]. TARGRETIN is a member of the retinoid class of drugs that is associated with birth defects in humans [see Use In Specific Populations (8.1)].

- Advise females of reproductive potential that they must avoid pregnancy while taking TARGRETIN and for at least 1 month following discontinuation of therapy.
- Advise females of reproductive potential of the importance of monthly pregnancy testing while taking TARGRETIN.
- Advise females of reproductive potential to use effective contraception for 1 month prior to the initiation of therapy, during therapy, and for at least 1 month following discontinuation of therapy and that two reliable forms of contraception should be used simultaneously, one of which should be non-hormonal.
- Advise females of reproductive potential that TARGRETIN therapy should be initiated on the second or third day of a normal menstrual period.
- Instruct patient to immediately stop taking TARGRETIN if she becomes pregnant while taking this drug.
- Advise male patients with sexual partners who are pregnant, possibly pregnant, or who could become pregnant that they must use condoms during sexual intercourse while taking TARGRETIN and for at least 1 month after the last dose of the drug.

Pancreatitis

Advise patients of the risk of developing pancreatitis, which may be accompanied by nausea, vomiting, and abdominal or back pain and to immediately contact their healthcare provider if these symptoms occur [see Warnings and Precautions (5.2)].

Hepatotoxicity

Inform patients of the possibility of developing liver function abnormalities and serious hepatic toxicity. Advise patients to immediately contact their healthcare provider if signs of liver failure occur, including jaundice, anorexia, bleeding, or bruising [see Warnings and Precautions (5.3)].

Neutropenia

Advise patients of the possibility of developing neutropenia and to immediately contact their healthcare provider should they develop a fever, particularly in association with any suggestion of infection [see Warnings and Precautions (5.5)].

Cataracts

Advise patients of the possibility of developing new or worsening cataracts and to inform their healthcare provider about any changes in their vision during treatment with TARGRETIN [see Warnings and Precautions (5.6)].

Vitamin A Supplementation Hazard

Advise patients to limit vitamin A intake to ≤15,000 IU/day to avoid potential additive toxic effects.

Hypoglycemia and Diabetes Mellitus

Advise patients of the possibility of developing hypoglycemia when using insulin, agents enhancing insulin secretion, or insulin sensitizers while on TARGRETIN therapy. Instruct patients on these medications to check their blood sugar frequently and to notify their physicians of any changes in blood sugar level [see Warnings and Precautions (5.8)].

Photosensitivity

Advise patients of potential increased skin sensitivity to sunlight while taking TARGRETIN and to minimize exposure to sunlight and artificial ultraviolet light [see Warnings and Precautions (5.9)].

Laboratory Tests

Advise patients of laboratory testing which will occur during therapy to monitor lipids, liver function, thyroid function, and white blood cell counts [see Warnings and Precautions (5.10)]. If applicable, advise patients of monthly pregnancy testing [see Use In Specific Populations (8.3)].

Administration Instructions

Advise patients to take TARGRETIN with a meal [see DOSAGE AND ADMINISTRATION].

Distributed by:

Bausch Health US, LLC

Bridgewater, NJ 08807 USA

Manufactured by:

Catalent Pharma Solutions LLC

St. Petersburg, FL 33716 USA

TARGRETIN is a trademark of Bausch Health Companies Inc. or its affiliates.

Any other product/brand names are trademarks of their respective owners.

© 2020 Bausch Health Companies Inc. or its affiliates

9436601

Patient Information

TARGRETIN® (tar-GRET-in)

(bexarotene)

Capsules

What is the most important information I should know about TARGRETIN?

TARGRETIN can cause serious side effects, including major birth defects to an unborn baby, if taken during pregnancy.

For females who can become pregnant:

- You should avoid becoming pregnant during treatment with TARGRETIN.
- Do not take TARGRETIN if you are pregnant or plan to become pregnant.
- Your healthcare provider will do a pregnancy test, within 1 week before you start TARGRETIN, and each month during treatment with TARGRETIN to make sure that you are not pregnant.
- You must use two effective forms of birth control together starting 1 month before you begin treatment with TARGRETIN, during treatment, and for 1 month after stopping TARGRETIN. Birth control pills (oral contraceptives) and other hormonal forms of birth control may not be effective if used with TARGRETIN. At least one of the forms of birth control that you choose should not contain hormones. Talk to your healthcare provider about what forms of birth control may be right for you during treatment with TARGRETIN.
- You should start taking TARGRETIN on the second or third day of a normal menstrual period. Follow your healthcare provider’s instructions about when to start TARGRETIN.
- Call your healthcare provider right away, if you become pregnant or think that you are pregnant during treatment with TARGRETIN, and for 1 month after you stop taking TARGRETIN.

For males:

- You must use a condom with female partners who are pregnant, might be pregnant, or who are able to become pregnant, during treatment with TARGRETIN and for at least 1 month after your last dose.

What is TARGRETIN?

TARGRETIN is a prescription medicine used to treat the skin problems that happen with a type of cancer called cutaneous T-cell lymphoma (CTCL) after treatment with at least one other type of medicine by mouth or injection, did not work or has stopped working.

It is not known if TARGRETIN is safe and effective in children.

Who should not take TARGRETIN?

Do not take TARGRETIN:

- if you are pregnant or plan to become pregnant. See “What is the most important information I should know about TARGRETIN?”
- if you are allergic to bexarotene or any of the ingredients in TARGRETIN. See the end of this leaflet for a complete list of ingredients in TARGRETIN.

Before taking TARGRETIN, tell your healthcare provider about all of your medical conditions, including if you:

- have or have had problems with your pancreas, including pancreatitis
- have or have had gallbladder problems
- have or have had liver problems
- have thyroid problems
- have diabetes
- have high levels of fats (lipids) called cholesterol or triglycerides in your blood
- have cataracts or a history of cataracts
- drink alcohol
- are pregnant, plan to become pregnant, or think you may be pregnant. See “What is the most important information I should know about TARGRETIN?”
- are breastfeeding or plan to breastfeed. It is not known if TARGRETIN passes into your breast milk. You should not breastfeed during treatment with TARGRETIN. Talk to your healthcare provider about the best way to feed your baby during treatment with TARGRETIN.

Tell your healthcare provider about all of the medicines you take, including prescription and over-the-counter medicines, vitamins, and herbal supplements. Using TARGRETIN with certain other medicines can affect each other.

How should I take TARGRETIN?

- Take TARGRETIN exactly as your healthcare provider tells you.
- Your healthcare provider will tell you how many TARGRETIN capsules to take each day. Your healthcare provider may change your daily dose of TARGRETIN as needed to treat your CTCL or if you get certain side effects. You should not change your dose unless your healthcare provider tells you to.

Take your dose of TARGRETIN one time a day with a meal. Your healthcare provider will do blood tests before you start TARGRETIN and during treatment to check for side effects.

What should I avoid while taking TARGRETIN?

- Limit your exposure to sunlight and artificial types of sunlight. TARGRETIN can make your skin more sensitive to sunlight and you can get sunburn.
- Limit the amount of vitamin A that you take during treatment with TARGRETIN. Large doses of vitamin A may cause side effects that are similar to side effects that can happen in people who take TARGRETIN.

What are the possible side effects of TARGRETIN?

TARGRETIN can cause serious side effects, including:

- See “What is the most important information I should know about TARGRETIN?”
- Increased levels of fats (lipids) called cholesterol or triglycerides, in your blood are common with TARGRETIN, but can also be serious. Your healthcare provider may prescribe you medicines to treat high cholesterol or triglycerides levels, reduce your dose, temporarily stop treatment or completely stop treatment with TARGRETIN if you have this problem.
- Inflammation of the pancreas (acute pancreatitis). TARGRETIN can sometimes cause pancreatitis that comes on suddenly (acute), and that can lead to death. Your risk of developing acute pancreatitis may be greater if you:
  - have had pancreatitis in the past
  - high levels of fats in your blood that are not controlled
  - drink large amounts of alcohol
  - have gallbladder problems
  - have diabetes that is not controlled
  - take certain medicines that can increase the amount of triglycerides in your blood
  - take medicines that can harm your pancreas

Tell your healthcare provider right away if you develop signs or symptoms of pancreatitis during treatment with TARGRETIN, including:

  - nausea that will not go away
  - vomiting
  - stomach-area (abdominal) or back pain
- Liver problems, including liver failure. TARGRETIN can cause increased liver function blood test results, or liver problems that can lead to death.
- Thyroid problems (hypothyroidism) are common with TARGRETIN. Your healthcare provider may prescribe thyroid hormone treatment for you if needed.
- Low white blood cell count is common with TARGRETIN, but may sometimes be severe.
- New or worse cataracts. Tell your healthcare provider about any changes in your vision during treatment with TARGRETIN. You may need to have an eye examination.
- Risk of low blood sugar in people who have diabetes. TARGRETIN can interact with certain medicines used to treat diabetes, such as insulin, sulfonylurea medicines, and thiazolinedione medicines. If you have diabetes, talk to your healthcare provider about your diabetes medicines and your risk for low blood sugar if you take TARGRETIN.

The most common side effects of TARGRETIN include:

- headache
- asthenia
- rash
- nausea
- infection
- stomach-area (abdomen) pain
- swelling of your hands, arms, feet or legs
- dry skin

These are not all the possible side effects of TARGRETIN. Call your doctor for medical advice about side effects. You may report side effects to FDA at 1-800-FDA-1088.

How should I store TARGRETIN?

- Store TARGRETIN between 36° to 77°F (2° to 25°C).
- Store the TARGRETIN bottle away from light, heat, and humidity.
- The capsules should not be taken after the expiration date printed on the bottle.

Keep TARGRETIN and all medicines out of the reach of children.

General information about the safe and effective use of TARGRETIN

Medicines are sometimes prescribed for purposes other than those listed in a Patient Information leaflet. Do not use TARGRETIN for a condition for which it was not prescribed. Do not give TARGRETIN to other people, even if they have the same symptoms that you have. It may harm them. You can ask your pharmacist or healthcare provider for information about TARGRETIN that is written for health professionals.

What are the ingredients in TARGRETIN?

Active ingredient: bexarotene

Inactive ingredients: butylated hydroxyanisole, polyethylene glycol 400, polysorbate 20, and povidone. The capsule shell contains gelatin, sorbitol special-glycerin blend, and titanium dioxide.

Distributed by: Bausch Health US, LLC, Bridgewater, NJ 08807 USA

Manufactured by: Catalent Pharma Solutions LLC, St. Petersburg, FL 33716 USA

TARGRETIN is a trademark of Bausch Health Companies Inc. or its affiliates.

Any other product/brand names are trademarks of their respective owners.

© 2020 Bausch Health Companies Inc. or its affiliates

For more information, call 1-800-321-4576.

This Patient Information has been approved by the U.S. Food and Drug Administration.

Rev. 04/2020

9436601

PACKAGE/LABEL PRINCIPAL DISPLAY PANEL – TARGRETIN – 75 mg Carton

NDC 0187-5526-75

Targretin®
(bexarotene) capsules

75 mg

100 Capsules

Rx Only

Bausch Health Companies